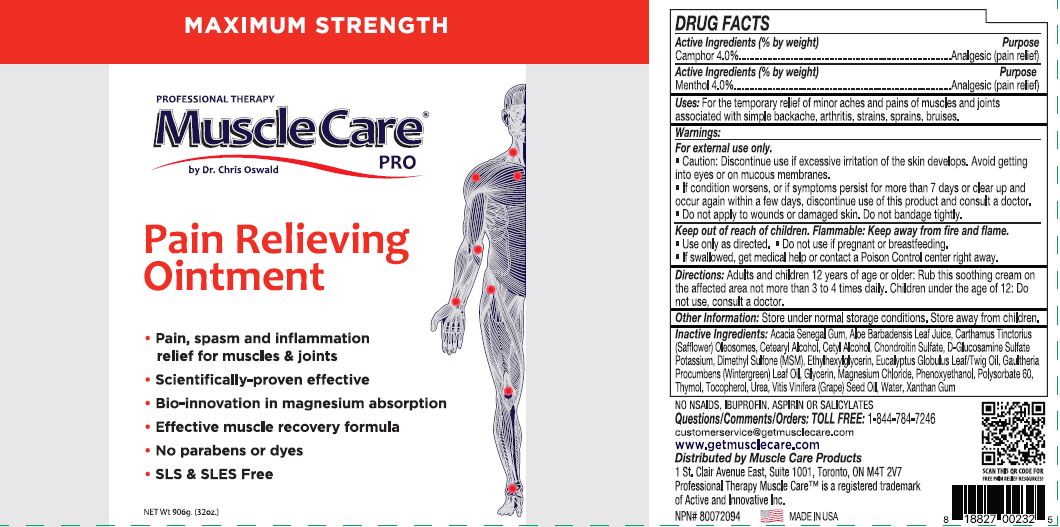 DRUG LABEL: Professional Therapy MuscleCare
NDC: 70039-303 | Form: CREAM
Manufacturer: ACTIVE AND INNOVATIVE, LLC
Category: otc | Type: HUMAN OTC DRUG LABEL
Date: 20240503

ACTIVE INGREDIENTS: CAMPHOR (SYNTHETIC) 4 g/100 g; MENTHOL 4 g/100 g
INACTIVE INGREDIENTS: ACACIA; ALOE VERA LEAF; CARTHAMUS TINCTORIUS (SAFFLOWER) OLEOSOMES; CETOSTEARYL ALCOHOL; CETYL ALCOHOL; CHONDROITIN SULFATE (BOVINE); GLUCOSAMINE SULFATE POTASSIUM CHLORIDE; DIMETHYL SULFONE; ETHYLHEXYLGLYCERIN; EUCALYPTUS OIL; METHYL SALICYLATE; GLYCERIN; MAGNESIUM CHLORIDE; PHENOXYETHANOL; POLYSORBATE 60; THYMOL; TOCOPHEROL; UREA; GRAPE SEED OIL; WATER; XANTHAN GUM

ACTIVE AND INNOVATIVE (as PLD) - MUSCLECARE OINTMENT (70039-303)

Active Ingredient (% by weight)

Camphor 4.0%
Menthol 4.0%

Purpose

Analgesic (pain relief)

Uses:

For the temporary relief of minor aches and pains of muscles and joints associated with simple backache, arthritis, strains, sprains, bruises.

Warnings:

For external use only.

- Caution: Discontinue use if excessive irritation of the skin develops. Avoid getting into eyes or on mucous membranes.
- If condition worsens, or if symptoms persist for more than 7 days or clear up and occur again within a few days, discontinue use of this product and consult a doctor.
- Do not apply to wounds or damaged skin. Do not bandage tightly.

Keep out of reach of children. Flammable: Keep away from fire and flame.

- Use only as directed
- Do not use if pregnant or breastfeeding
- If swallowed, get medical help or contact a Poison Control center right away

Directions:

Adults and children 12 years of age or older: Rub this soothing cream on the affected area not more than 3 to 4 times daily. Children under the age of 12: Do not use, consult a doctor.

Other Information:

Store under normal storage conditions. Store away from children.

Inactive Ingredients:

Acacia Senegal Gum, Aloe Barbadensis Leaf Juice, Carthamus Tinctorius (Safflower) Oleosomes, Cetearyl Alcohol, Cetyl Alcohol, Chondroitin Sulfate, D-Glucosamine Sulfate Potassium, Dimethyl Sulfone (MSM), Ethylhexylglycerin, Eucalyptus Globulus Leaf/Twig Oil, Gaultheria Procumbens (Wintergreen) Leaf Oil, Glycerin, Magnesium Chloride, Phenoxyethanol, Polysorbate 60, Thymol, Tocopherol, Urea, Vitis Vinifera (Grape) Seed Oil, Water, Xanthan Gum